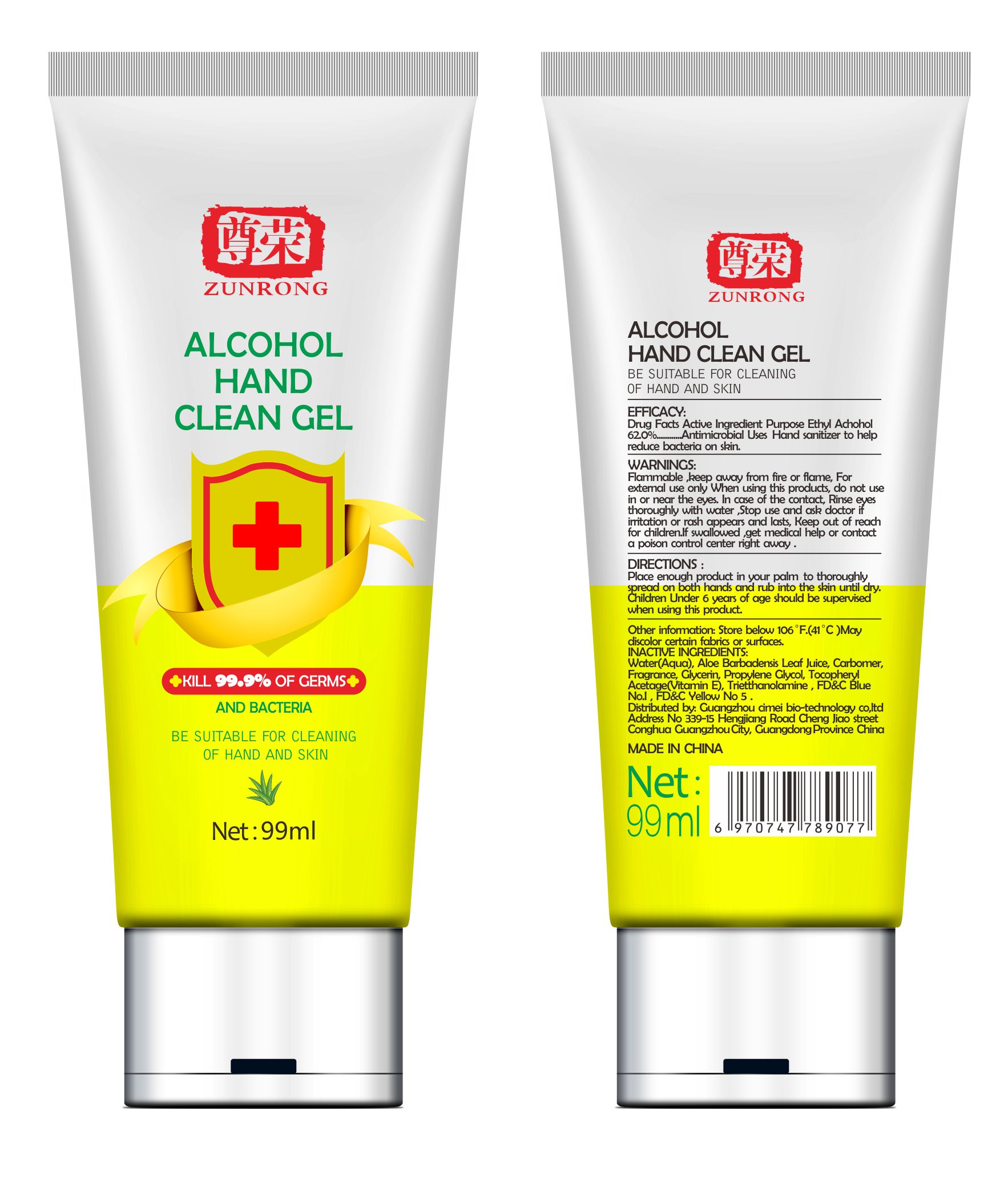 DRUG LABEL: H C
NDC: 75233-001 | Form: GEL
Manufacturer: Guangzhou cimei bio technology co.ltd
Category: otc | Type: HUMAN OTC DRUG LABEL
Date: 20200502

ACTIVE INGREDIENTS: ALCOHOL 62 mL/100 mL
INACTIVE INGREDIENTS: ALOE VERA LEAF; GLYCERIN; PROPYLENE GLYCOL; .ALPHA.-TOCOPHEROL; TROLAMINE; FD&C BLUE NO. 1; WATER; FD&C YELLOW NO. 5; CARBOMER HOMOPOLYMER, UNSPECIFIED TYPE

ALCOHOL HAND CLEAN GEL

Active Ingredient

Ethyl Achohol 62.0%

Purpose

Antimicrobial

Uses

Hand sanitizer to help reduce bacteria on skin.

WARNINGS

Flammable, keep away from fire or flame, For external use only When using this products,do not use in or near the eyes.In case of the contact,Rinse eyes thoroughly with water, Stop use and ask doctor if irritation or rash appears and lasts, Keep out of reach for children.If swallowed, get medical help or contact a poison control center right away.

DIRECTIONS

Place enough product in your palm to thoroughly spread on both hands and rub into the skin until dry.

Children Under 6 years of age should be supervised when using this product.

Other information

Store below 106°F.(41°C)

May discolor certain fabrics or surfaces.

INACTIVE INGREDIENTS

Water(Aqua),Aloe Barbadensis Leaf Juice, Carbomer,Fragrance,Glycerin, Propylene Glycol, Tocopheryl Acetage(Vitamin E),

Triethanolamine,FD&C Blue NO.1,FD&C Yellow NO 5.